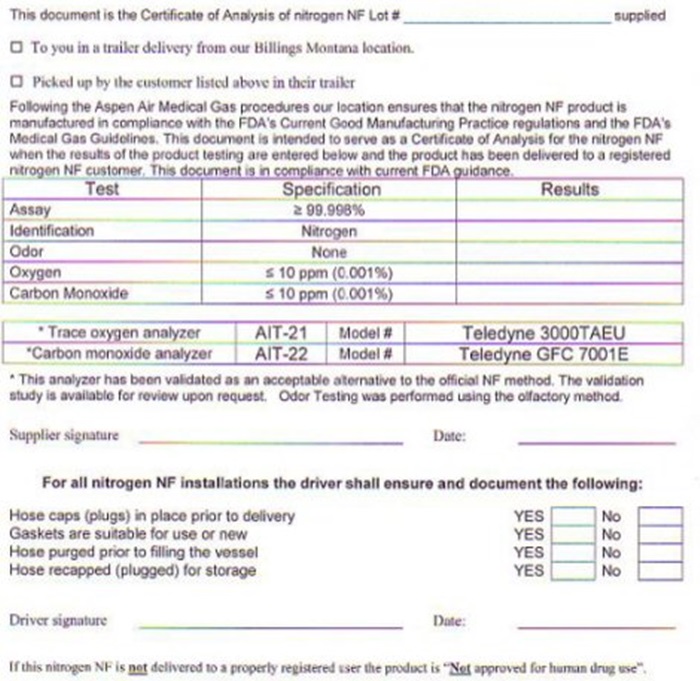 DRUG LABEL: NITROGEN
NDC: 42914-010 | Form: GAS
Manufacturer: Aspen Air U.S., LLC
Category: prescription | Type: HUMAN PRESCRIPTION DRUG LABEL
Date: 20241010

ACTIVE INGREDIENTS: NITROGEN 99 L/100 L

Nitrogen

NITROGEN CERTIFICATE OF ANALYSIS

Customer

_______ Aspen Air

________ 1524 Lockwood Road

________ Billings, MT

This document is the Certificate of Analysis of nitrogen NF Lot # ______________ supplied

___ To you is a trailer delivery from our Billings Montana location.

___ Picked up by the customer listed above in their trailer

Following the Aspen Air Medical Gas procedures our location ensures that the nitrogen NF product is manufactured in compliance with the FDA’s Current Good Manufacturing Practice regulations and the FDA’s Medical Gas Guidelines. This document is intended to serve as a Certificate of Analysis for the nitrogen NF when the results of the product testing are entered below and the product has been delivered to a registered nitrogen NF customer. This document is in compliance with current FDA guidance.

Test Specification Results

Assay ≥ 99.998% ____

Identification Nitrogen ____

Odor None ____

Oxygen ≤ 10 ppm (0.001%) ____

Carbon Monoxide ≤ 10 ppm (0.001%) ____

*Trace oxygen analyzer AIT-21 Model# Teledyne 3000TAEU

*Carbon monoxide analyzer AIT-22 Model# Teledyne GFC 7001E

*This analyzer has been validated as an acceptable alternative to the official NF method. The validation study is available for review upon request. Odor Testing was performed using the olfactory method.

Supplier signature: __________________________ Date: ____________

For all nitrogen NF installations, the driver shall ensure and document the following:

Hose caps (plugs) in place prior to delivery Yes ___ No ___

Gaskets are suitable for use or new Yes ___ No ___

Hose purged prior to filling the vessel Yes ___ No ___

Hose recapped (plugged) for storage Yes ___ No ___

Driver signature: ___________________ Date: ________________

If this nitrogen NF is not delivered to a properly registered user the product is “Not approved for human drug use”.